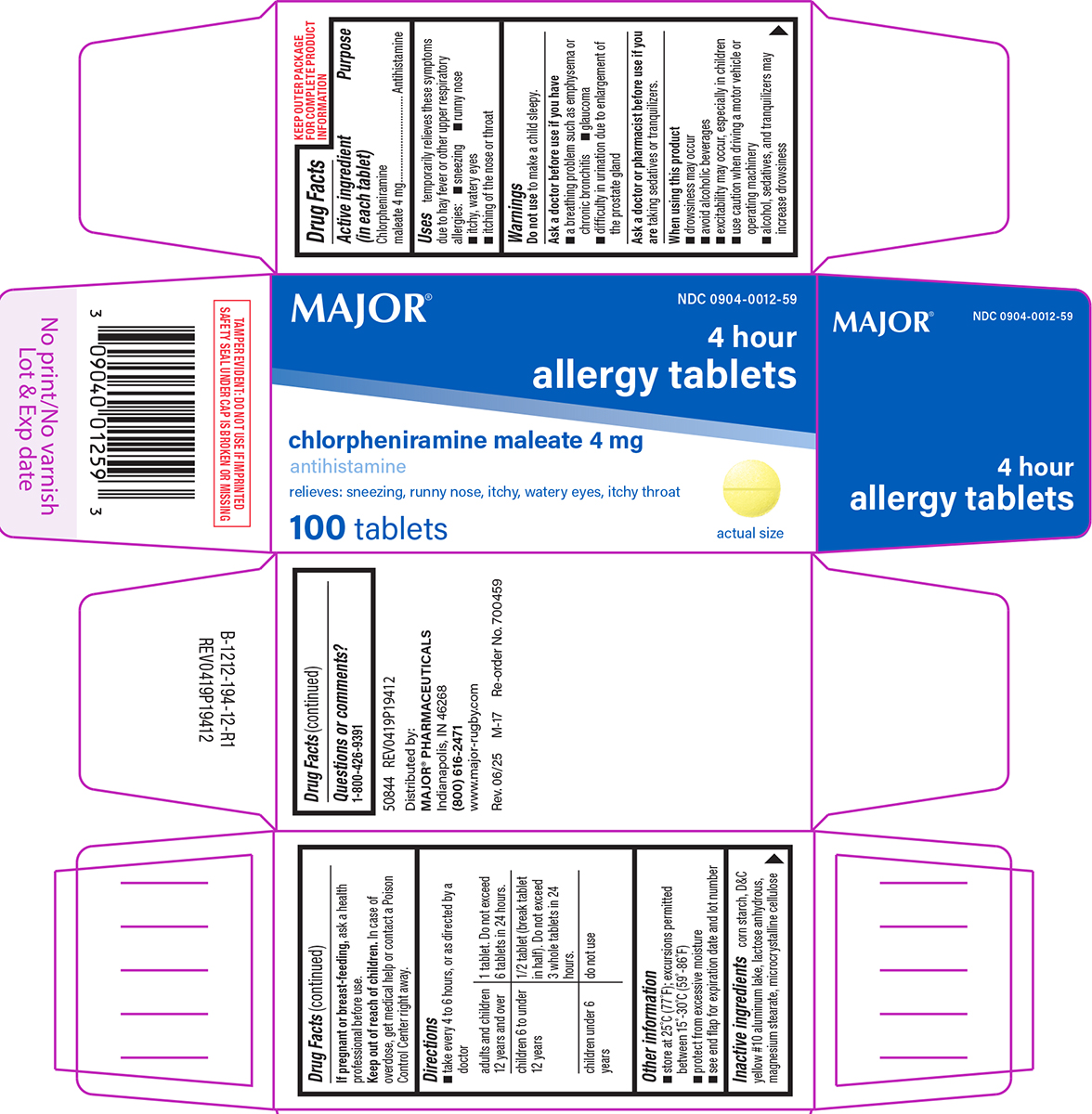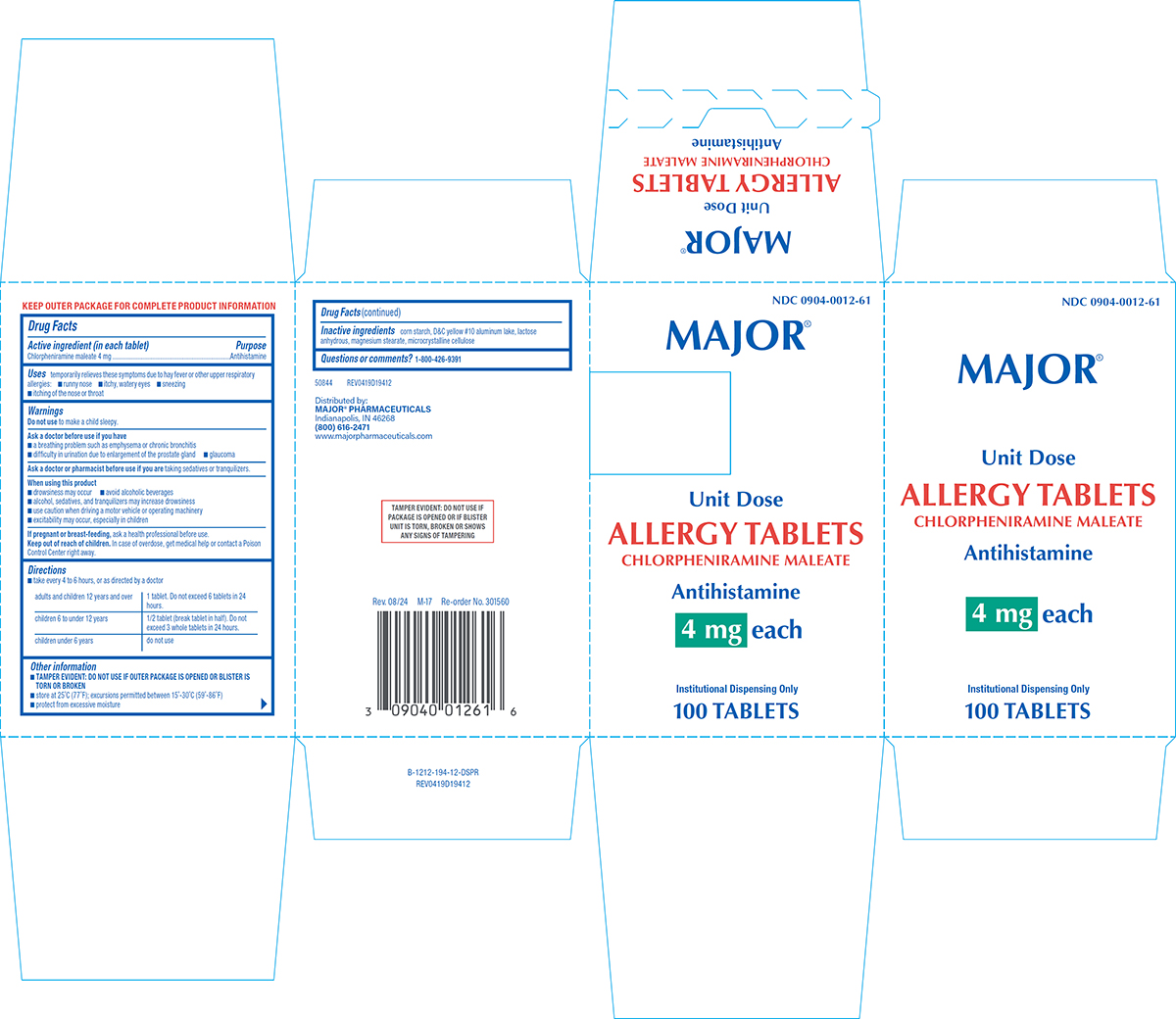 DRUG LABEL: Allergy
NDC: 0904-0012 | Form: TABLET
Manufacturer: Major Pharmaceuticals
Category: otc | Type: HUMAN OTC DRUG LABEL
Date: 20250804

ACTIVE INGREDIENTS: CHLORPHENIRAMINE MALEATE 4 mg/1 1
INACTIVE INGREDIENTS: STARCH, CORN; D&C YELLOW NO. 10 ALUMINUM LAKE; ANHYDROUS LACTOSE; MAGNESIUM STEARATE; MICROCRYSTALLINE CELLULOSE

Major 44-194

Active ingredient (in each tablet)

Chlorpheniramine maleate 4 mg

Purpose

Antihistamine

Uses

temporarily relieves these symptoms due to hay fever or other upper respiratory allergies:

- runny nose
- itchy, watery eyes
- sneezing
- itching of the nose or throat

Warnings

Do not use

to make a child sleepy.

Ask a doctor before use if you have

- a breathing problem such as emphysema or chronic bronchitis
- glaucoma
- difficulty in urination due to enlargement of the prostate gland

Ask a doctor or pharmacist before use if you are

taking sedatives or tranquilizers.

When using this product

- drowsiness may occur
- avoid alcoholic beverages
- alcohol, sedatives, and tranquilizers may increase drowsiness
- use caution when driving a motor vehicle or operating machinery
- excitability may occur, especially in children

If pregnant or breast-feeding,

ask a health professional before use.

Keep out of reach of children.

In case of overdose, get medical help or contact a Poison Control Center right away.

Directions

- take every 4 to 6 hours, or as directed by a doctor

adults and children 12 years and over | 1 tablet. Do not exceed 6 tablets in 24 hours.
children 6 to under 12 years | 1/2 tablet (break tablet in half). Do not exceed 3 whole tablets in 24 hours.
children under 6 years | do not use

Other information

- see end flap for expiration date and lot number
- store at 25°C (77°F); excursions permitted between 15°-30°C (59°-86°F)
- protect from excessive moisture

Inactive ingredients

corn starch, D&C yellow #10 aluminum lake, lactose anhydrous, magnesium stearate, microcrystalline cellulose

Questions or comments?

1-800-426-9391

Principal Display Panel

NDC 0904-0012-59

MAJOR®

4 hour
allergy tablets
chlorpheniramine maleate 4 mg
antihistamine

relieves: sneezing, runny nose, itchy, watery eyes, itchy throat

actual size

100 tablets

TAMPER EVIDENT: DO NOT USE IF IMPRINTED
SAFETY SEAL UNDER CAP IS BROKEN OR MISSING

50844 REV0419P19412

Distributed by:
MAJOR® PHARMACEUTICALS
Indianapolis, IN 46268
(800) 616-2471
www.major-rugby.com

Rev. 06/25 M-17 Re-order No. 700459

Major 44-194

Principal Display Panel - Unit Dose

NDC 0904-0012-61

MAJOR®

Unit Dose

ALLERGY TABLETS
CHLORPHENIRAMINE MALEATE

Antihistamine

4 mg each

Institutional Dispensing Only
100 TABLETS

TAMPER EVIDENT: DO NOT USE IF
PACKAGE IS OPENED OR IF BLISTER
UNIT IS TORN, BROKEN OR SHOWS
ANY SIGNS OF TAMPERING

50844 REV0419D19412

Distributed by:
MAJOR® PHARMACEUTICALS
Indianapolis, IN 46268
(800) 616-2471
www.majorpharmaceuticals.com

Rev. 08/24 M-17 Re-order No. 301560

Major 44-194-DSP